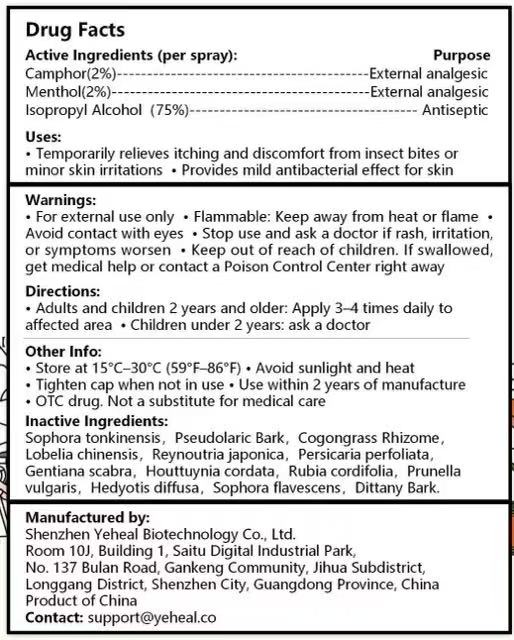 DRUG LABEL: Yeheal
NDC: 87008-813 | Form: SPRAY
Manufacturer: Shenzhen Yeheal Biotechnology Co., Ltd
Category: otc | Type: HUMAN OTC DRUG LABEL
Date: 20250822

ACTIVE INGREDIENTS: CAMPHOR, (-)- 2 mg/100 mg; MENTHOL 2 mg/100 mg; ISOPROPYL ALCOHOL 75 mg/100 mg
INACTIVE INGREDIENTS: REYNOUTRIA JAPONICA WHOLE; RUBIA CORDIFOLIA WHOLE; OLDENLANDIA HERBACEA WHOLE; PERSICARIA PERFOLIATA WHOLE; HOUTTUYNIA CORDATA WHOLE; DICTAMNUS DASYCARPUS WHOLE; GENTIANA SCABRA WHOLE; IMPERATA CYLINDRICA ROOT; PRUNELLA VULGARIS; SOPHORA TONKINENSIS ROOT; PSEUDOLARIX AMABILIS BARK; SOPHORA FLAVESCENS WHOLE

ACTIVE INGREDIENT

Camphor(2%)-----External analgesic
Menthol(2%)---External analgesic
Isopropyl Alcohol(75%)----------- Antiseptic

Keep out of reach of children.

WARNINGS

For external use only
Flammable: Keep away from heat or flameAvoid contact with eyes .
Stop use and ask a doctor if rash, irritationor symptoms worsen
Keep out of reach of children.
lf swallowedget medical help or contact a Poison Control Center right away

DOSAGE AND ADMINISTRATION

Adults and children 2 years and older: Apply 3 to 4 times daily to the affected area.
Children under 2 years: Ask a doctor.

INACTIVE INGREDIENT

Sophora tonkinensis, Pseudolaric Bark,Cogongrass RhizomeLobelia chinensis, Reynoutria japonica, Persicaria perfoliata,Gentiana scabra, Houttuynia cordata, Rubia cordifolia, Prunellavulgaris, Hedyotis diffusa, Sophora flavescens, Dittany Bark.

OTHER SAFETY INFORMATION

Store at 15°C-30°C(59°F-86°F)*Avoid sunlight and heat.

Tighten cap when not in use .

Use within 2 years of manufacture.

OTC drug. Not a substitute for medical care

PURPOSE

External analgesic

Antiseptic

INDICATIONS AND USAGE

Temporarily relieves itching and discomfort from insect bites orminor skin irritations ,Provides mild antibacterial effect for skin